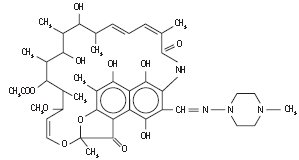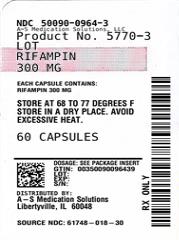 DRUG LABEL: Rifampin
NDC: 50090-0964 | Form: CAPSULE
Manufacturer: A-S Medication Solutions
Category: prescription | Type: HUMAN PRESCRIPTION DRUG LABEL
Date: 20210824

ACTIVE INGREDIENTS: RIFAMPIN 300 mg/1 1
INACTIVE INGREDIENTS: LACTOSE MONOHYDRATE; SODIUM LAURYL SULFATE; TALC; SILICON DIOXIDE; MAGNESIUM STEARATE; AMMONIA; ISOPROPYL ALCOHOL; BUTYL ALCOHOL; SHELLAC; PROPYLENE GLYCOL; DIMETHICONE; TITANIUM DIOXIDE; STARCH, CORN; FD&C BLUE NO. 1; FD&C RED NO. 40; GELATIN, UNSPECIFIED

RIFAMPIN CAPSULES, USP

Rx Only
Rev. 11/18

To reduce the development of drug-resistant bacteria and maintain the effectiveness of rifampin capsules USP and other antibacterial drugs, rifampin should be used only to treat or prevent infections that are proven or strongly suspected to be caused by bacteria.

DESCRIPTION

Rifampin capsules, USP for oral administration contain 150 mg or 300 mg rifampin per capsule. The 150 mg and 300 mg capsules also contain, as inactive ingredients: colloidal silicon dioxide, corn starch, FD&C Blue No. 1, FD&C Red No. 40, gelatin, lactose monohydrate, magnesium stearate, sodium lauryl sulfate, talc, and titanium dioxide.

The printing ink contains ammonium hydroxide, isopropyl alcohol, n-butyl alcohol, pharmaceutical glaze, propylene glycol, simethicone, and titanium dioxide

Rifampin is a semisynthetic antibiotic derivative of rifamycin SV. Rifampin is a red-brown crystalline powder very slightly soluble in water at neutral pH, freely soluble in chloroform, soluble in ethyl acetate and in methanol. Its molecular weight is 822.95 and its chemical formula is C43H58N4O12.

The chemical name for rifampin is either:

3-[[(4-Methyl-1-piperazinyl)imino]methyl]rifamycin

or

5,6,9,17,19,21-hexahydroxy-23-methoxy-2,4,12,16,20,22-heptamethyl-8-[N-(4-methyl-1-piperazinyl)formimidoyl]-2,7-(epoxypentadeca[1,11,13]trienimino)naphtho[2,1-b]furan-1,11(2H)-dione 21-acetate.

Its structural formula is:

CLINICAL PHARMACOLOGY

Oral Administration

Rifampin is readily absorbed from the gastrointestinal tract. Peak serum concentrations in healthy adults and pediatric populations vary widely from individual to individual. Following a single 600 mg oral dose of rifampin in healthy adults, the peak serum concentration averages 7 mcg/mL but may vary from 4 to 32 mcg/mL. Absorption of rifampin is reduced by about 30% when the drug is ingested with food.

Rifampin is widely distributed throughout the body. It is present in effective concentrations in many organs and body fluids, including cerebrospinal fluid. Rifampin is about 80% protein bound. Most of the unbound fraction is not ionized and, therefore, diffuses freely into tissues.

In healthy adults, the mean biological half-life of rifampin in serum averages 3.35 ± 0.66 hours after a 600 mg oral dose, with increases up to 5.08 ± 2.45 hours reported after a 900 mg dose. With repeated administration, the half-life decreases and reaches average values of approximately 2 to 3 hours. The half-life does not differ in patients with renal failure at doses not exceeding 600 mg daily, and consequently, no dosage adjustment is required. The half-life of rifampin at a dose of 720 mg daily has not been established in patients with renal failure. Following a single 900 mg oral dose of rifampin in patients with varying degrees of renal insufficiency, the mean half-life increased from 3.6 hours in healthy adults to 5.0, 7.3, and 11.0 hours in patients with glomerular filtration rates of 30 to 50 mL/min, less than 30 mL/min, and in anuric patients, respectively. Refer to the WARNINGS section for information regarding patients with hepatic insufficiency.

After absorption, rifampin is rapidly eliminated in the bile, and an enterohepatic circulation ensues. During this process, rifampin undergoes progressive deacetylation so that nearly all the drug in the bile is in this form in about 6 hours. This metabolite has antibacterial activity. Intestinal reabsorption is reduced by deacetylation, and elimination is facilitated. Up to 30% of a dose is excreted in the urine, with about half of this being unchanged drug.

Pediatrics

Oral Administration

In one study, pediatric patients 6 to 58 months old were given rifampin suspended in simple syrup or as dry powder mixed with applesauce at a dose of 10 mg/kg body weight. Peak serum concentrations of 10.7 ± 3.7 and 11.5 ± 5.1 mcg/mL were obtained 1 hour after preprandial ingestion of the drug suspension and the applesauce mixture, respectively. After the administration of either preparation, the t1/2 of rifampin averaged 2.9 hours. It should be noted that in other studies in pediatric populations, at doses of 10 mg/kg body weight, mean peak serum concentrations of 3.5 mcg/mL to 15 mcg/mL have been reported.

Microbiology

Mechanism of Action

Rifampin inhibits DNA-dependent RNA polymerase activity in susceptible Mycobacterium tuberculosis organisms. Specifically, it interacts with bacterial RNA polymerase but does not inhibit the mammalian enzyme.

Resistance

Organisms resistant to rifampin are likely to be resistant to other rifamycins. In addition, resistance to rifampin has been determined to occur as single-step mutations of the DNA-dependent RNA polymerase. Since resistance can emerge rapidly, appropriate susceptibility tests should be performed in the event of persistent positive cultures.

Activity in vitro and in vivo

Rifampin has bactericidal activity in vitro against slow and intermittently growing M tuberculosis organisms.

Rifampin has been shown to be active against most strains of the following microorganisms, both in vitro and in clinical infections as described in the INDICATIONS AND USAGE section.

Aerobic Gram-Negative Microorganisms:
Neisseria meningitidis

"Other" Microorganisms:
Mycobacterium tuberculosis

The following in vitro data are available, but their clinical significance is unknown.

Rifampin exhibits in vitro activity against most strains of the following microorganisms; however, the safety and effectiveness of rifampin in treating clinical infections due to these microorganisms have not been established in adequate and well-controlled trials.

Aerobic Gram-Positive Microorganisms:
Staphylococcus aureus (including Methicillin-Resistant S. aureus/MRSA)
Staphylococcus epidermidis

Aerobic Gram-Negative Microorganisms:
Haemophilus influenzae

"Other" Microorganisms:
Mycobacterium leprae

β-lactamase production should have no effect on rifampin activity.

Susceptibility Testing

For specific information regarding susceptibility test criteria and associated test methods and quality control standards recognized by FDA for this drug, please see: www.fda.gov/STIC.

INDICATIONS AND USAGE

In the treatment of both tuberculosis and the meningococcal carrier state, the small number of resistant cells present within large populations of susceptible cells can rapidly become the predominant type. Bacteriologic cultures should be obtained before the start of therapy to confirm the susceptibility of the organism to rifampin and they should be repeated throughout therapy to monitor the response to treatment. Since resistance can emerge rapidly, susceptibility tests should be performed in the event of persistent positive cultures during the course of treatment. If test results show resistance to rifampin and the patient is not responding to therapy, the drug regimen should be modified.

Tuberculosis

Rifampin is indicated in the treatment of all forms of tuberculosis.

A three-drug regimen consisting of rifampin, isoniazid, and pyrazinamide [e.g., RIFATER®]^1 is recommended in the initial phase of short-course therapy which is usually continued for 2 months. The Advisory Council for the Elimination of Tuberculosis, the American Thoracic Society, and Centers for Disease Control and Prevention recommend that either streptomycin or ethambutol be added as a fourth drug in a regimen containing isoniazid (INH), rifampin, and pyrazinamide for initial treatment of tuberculosis unless the likelihood of INH resistance is very low. The need for a fourth drug should be reassessed when the results of susceptibility testing are known. If community rates of INH resistance are currently less than 4%, an initial treatment regimen with less than four drugs may be considered.

Following the initial phase, treatment should be continued with rifampin and isoniazid [e.g., RIFAMATE®]^2 for at least 4 months. Treatment should be continued for longer if the patient is still sputum or culture positive, if resistant organisms are present, or if the patient is HIV positive.

Meningococcal Carriers

Rifampin is indicated for the treatment of asymptomatic carriers of Neisseria meningitidis to eliminate meningococci from the nasopharynx. Rifampin is not indicated for the treatment of meningococcal infection because of the possibility of the rapid emergence of resistant organisms. (See WARNINGS).

Rifampin should not be used indiscriminately, and therefore, diagnostic laboratory procedures, including serotyping and susceptibility testing, should be performed for establishment of the carrier state and the correct treatment. So that the usefulness of rifampin in the treatment of asymptomatic meningococcal carriers is preserved, the drug should be used only when the risk of meningococcal disease is high.

To reduce the development of drug-resistant bacteria and maintain the effectiveness of rifampin and other antibacterial drugs, rifampin should be used only to treat or prevent infections that are proven or strongly suspected to be caused by susceptible bacteria. When culture and susceptibility information are available, they should be considered in selecting or modifying antibacterial therapy. In the absence of such data, local epidemiology and susceptibility patterns may contribute to the empiric selection of therapy.

CONTRAINDICATIONS

Rifampin is contraindicated in patients with a history of hypersensitivity to rifampin or any of the components, or to any of the rifamycins. (See WARNINGS).

Rifampin is contraindicated in patients who are also receiving ritonavir-boosted saquinavir due to an increased risk of severe hepatocellular toxicity. (See PRECAUTIONS, Drug Interactions.)

Rifampin is contraindicated in patients who are also receiving atazanavir, darunavir, fosamprenavir, saquinavir, or tipranavir due to the potential of rifampin to substantially decrease plasma concentrations of these antiviral drugs, which may result in loss of antiviral efficacy and/or development of viral resistance.

WARNINGS

Rifampin has been shown to produce liver dysfunction. Fatalities associated with jaundice have occurred in patients with liver disease and in patients taking rifampin with other hepatotoxic agents. Patients with impaired liver function should be given rifampin only in cases of necessity and then with caution and under strict medical supervision. In these patients, careful monitoring of liver function, especially SGPT/ALT and SGOT/AST should be carried out prior to therapy and then every 2 to 4 weeks during therapy. If signs of hepatocellular damage occur, rifampin should be withdrawn.

In some cases, hyperbilirubinemia resulting from competition between rifampin and bilirubin for excretory pathways of the liver at the cell level can occur in the early days of treatment. An isolated report showing a moderate rise in bilirubin and/or transaminase level is not in itself an indication for interrupting treatment; rather, the decision should be made after repeating the tests, noting trends in the levels, and considering them in conjunction with the patient's clinical condition.

Rifampin has enzyme-inducing properties, including induction of delta amino levulinic acid synthetase. Isolated reports have associated porphyria exacerbation with rifampin administration.

The possibility of rapid emergence of resistant meningococci restricts the use of rifampin to short-term treatment of the asymptomatic carrier state. Rifampin is not to be used for the treatment of meningococcal disease.

Systemic hypersensitivity reactions, including Drug Reaction with Eosinophilia and Systemic Symptoms

(DRESS) syndrome, may occur in patients receiving rifampin (see ADVERSE REACTIONS). Signs and symptoms of hypersensitivity reactions may include fever, rash, urticaria, angioedema, hypotension, acute bronchospasm, conjunctivitis, thrombocytopenia, neutropenia, elevated liver transaminases or flu-like syndrome (weakness, fatigue, muscle pain, nausea, vomiting, headache, chills, aches, itching, sweats, dizziness, shortness of breath, chest pain, cough, syncope, palpitations). These reactions may be severe and DRESS may be fatal. Manifestations of hypersensitivity, such as fever, lymphadenopathy or laboratory abnormalities (including eosinophilia, liver abnormalities) may be present even though rash is not evident. Monitor patients receiving rifampin for signs and/or symptoms of hypersensitivity reactions. If these signs or symptoms occur, discontinue rifampin and administer supportive measures.

PRECAUTIONS

General

Rifampin should be used with caution in patients with a history of diabetes mellitus, as diabetes management may be more difficult.

Prescribing rifampin in the absence of a proven or strongly suspected bacterial infection or a prophylactic indication is unlikely to provide benefit to the patient and increases the risk of the development of drug-resistant bacteria.

For the treatment of tuberculosis, rifampin is usually administered on a daily basis. Doses of rifampin greater than 600 mg given once or twice weekly have resulted in a higher incidence of adverse reactions, including the "flu syndrome" (fever, chills and malaise), hematopoietic reactions (leukopenia, thrombocytopenia, or acute hemolytic anemia), cutaneous, gastrointestinal, and hepatic reactions, shortness of breath, shock, anaphylaxis, and renal failure. Recent studies indicate that regimens using twice-weekly doses of rifampin 600 mg plus isoniazid 15 mg/kg are much better tolerated.

Rifampin is not recommended for intermittent therapy; the patient should be cautioned against intentional or accidental interruption of the daily dosage regimen since rare renal hypersensitivity reactions have been reported when therapy was resumed in such cases.

Rifampin has enzyme induction properties that can enhance the metabolism of endogenous substrates including adrenal hormones, thyroid hormones, and vitamin D. Rifampin and isoniazid have been reported to alter vitamin D metabolism. In some cases, reduced levels of circulating 25-hydroxy vitamin D and 1,25-dihydroxy vitamin D have been accompanied by reduced serum calcium and phosphate, and elevated parathyroid hormone.

Information for Patients

Patients should be counseled that antibacterial drugs including rifampin should only be used to treat bacterial infections. They do not treat viral infections (e.g., the common cold). When rifampin is prescribed to treat a bacterial infection, patients should be told that although it is common to feel better early in the course of therapy, the medication should be taken exactly as directed. Skipping doses or not completing the full course of therapy may (1) decrease the effectiveness of the immediate treatment and (2) increase the likelihood that bacteria will develop resistance and will not be treatable by rifampin or other antibacterial drugs in the future.

The patient should be told that rifampin may produce a discoloration (yellow, orange, red, brown) of the teeth, urine, sweat, sputum, and tears, and the patient should be forewarned of this. Soft contact lenses may be permanently stained.

The patient should be advised that the reliability of oral or other systemic hormonal contraceptives may be affected; consideration should be given to using alternative contraceptive measures.

Patients should be instructed to take rifampin either 1 hour before or 2 hours after a meal with a full glass of water.

Patients should be instructed to notify their physicians promptly if they experience any of the following: rash, fever, or swollen lymph nodes, loss of appetite, malaise, nausea and vomiting, darkened urine, yellowish discoloration of the skin and eyes, cough, shortness of breath, wheezing and pain or swelling of the joints.

Compliance with the full course of therapy must be emphasized, and the importance of not missing any doses must be stressed.

Laboratory Tests

Adults treated for tuberculosis with rifampin should have baseline measurements of hepatic enzymes, bilirubin, serum creatinine, a complete blood count, and a platelet count (or estimate). Baseline tests are unnecessary in pediatric patients unless a complicating condition is known or clinically suspected.

Patients should be seen at least monthly during therapy and should be specifically questioned concerning symptoms associated with adverse reactions. All patients with abnormalities should have follow-up, including laboratory testing, if necessary. Routine laboratory monitoring for toxicity in people with normal baseline measurements is generally not necessary.

Drug Interactions

Healthy subjects who received rifampin 600 mg once daily concomitantly with saquinavir 1000 mg/ritonavir 100 mg twice daily (ritonavir-boosted saquinavir) developed severe hepatocellular toxicity. Therefore, concomitant use of these medications is contraindicated. (See CONTRAINDICATIONS.)

Enzyme Induction: Rifampin is known to induce certain cytochrome P-450 enzymes. Administration of rifampin with drugs that undergo biotransformation through these metabolic pathways may accelerate elimination of coadministered drugs. To maintain optimum therapeutic blood levels, dosages of drugs metabolized by these enzymes may require adjustment when starting or stopping concomitantly administered rifampin.

Rifampin has been reported to substantially decrease the plasma concentrations of the following antiviral drugs: atazanavir, darunavir, fosamprenavir, saquinavir, and tipranavir. These antiviral drugs must not be co-administered with rifampin. (See CONTRAINDICATIONS.)

Rifampin has been reported to accelerate the metabolism of the following drugs: anticonvulsants (e.g., phenytoin), digitoxin, antiarrhythmics (e.g., disopyramide, mexiletine, quinidine, tocainide), oral anticoagulants, antifungals (e.g., fluconazole, itraconazole, ketoconazole), barbiturates, beta-blockers, calcium channel blockers (e.g., diltiazem, nifedipine, verapamil), chloramphenicol, clarithromycin, corticosteroids, cyclosporine, cardiac glycoside preparations, clofibrate, oral or other systemic hormonal contraceptives, dapsone, diazepam, doxycycline, fluoroquinolones (e.g., ciprofloxacin), haloperidol, oral hypoglycemic agents (sulfonylureas), levothyroxine, methadone, narcotic analgesics, progestins, quinine, tacrolimus, theophylline, tricyclic antidepressants (e.g., amitriptyline, nortriptyline) and zidovudine. It may be necessary to adjust the dosages of these drugs if they are given concurrently with rifampin.

Patients using oral or other systemic hormonal contraceptives should be advised to change to non-hormonal methods of birth control during rifampin therapy.

Rifampin has been observed to increase the requirements for anticoagulant drugs of the coumarin type. In patients receiving anticoagulants and rifampin concurrently, it is recommended that the prothrombin time be performed daily or as frequently as necessary to establish and maintain the required dose of anticoagulant.

Other Interactions: When the two drugs were taken concomitantly, decreased concentrations of atovaquone and increased concentrations of rifampin were observed.

Concurrent use of ketoconazole and rifampin has resulted in decreased serum concentrations of both drugs. Concurrent use of rifampin and enalapril has resulted in decreased concentrations of enalaprilat, the active metabolite of enalapril. Dosage adjustments should be made if indicated by the patient's clinical condition.

Concomitant antacid administration may reduce the absorption of rifampin. Daily doses of rifampin should be given at least 1 hour before the ingestion of antacids.

Probenecid and cotrimoxazole have been reported to increase the blood level of rifampin.

When rifampin is given concomitantly with either halothane or isoniazid, the potential for hepatotoxicity is increased. The concomitant use of rifampin and halothane should be avoided. Patients receiving both rifampin and isoniazid should be monitored close for hepatotoxicity.

Plasma concentrations of sulfapyridine may be reduced following the concomitant administration of sulfasalazine and rifampin. This finding may be the result of alteration in the colonic bacteria responsible for the reduction of sulfasalazine to sulfapyridine and mesalamine.

Drug/Laboratory Interactions

Cross-reactivity and false-positive urine screening tests for opiates have been reported in patients receiving rifampin when using the KIMS (Kinetic Interaction of Microparticles in Solution) method (e.g., Abuscreen OnLine opiates assay; Roche Diagnostic Systems). Confirmatory tests, such as gas chromatography/mass spectrometry, will distinguish rifampin from opiates.

Therapeutic levels of rifampin have been shown to inhibit standard microbiological assays for serum folate and vitamin B12. Thus, alternate assay methods should be considered. Transient abnormalities in liver function tests (e.g., elevation in serum bilirubin, alkaline phosphatase, and serum transaminases) and reduced biliary excretion of contrast media used for visualization of the gallbladder have also been observed. Therefore, these tests should be performed before the morning dose of rifampin.

Carcinogenesis, Mutagenesis, Impairment of Fertility

A few cases of accelerated growth of lung carcinoma have been reported in man, but a causal relationship with the drug has not been established. Hepatomas were increased in female (C3Hf/DP) mice dosed for 60 weeks with rifampicin followed by an observation period of 46 weeks, at 20 to 120 mg/kg (equivalent to 0.1 to 0.5 times the maximum dosage used clinically, based on body surface area comparisons). There was no evidence of tumorigenicity in male C3Hf/DP mice or in similar studies in BALB/c mice, or in two year studies in Wistar rats.

There was no evidence of mutagenicity in both prokaryotic (Salmonella typhi, Escherichia coli) and eukaryotic (Saccharomyces cerevisiae) bacteria, Drosophila melanogaster, or ICR/Ha Swiss mice. An increase in chromatid breaks was noted when whole blood cell cultures were treated with rifampin. Increased frequency of chromosomal aberrations was observed in vitro in lymphocytes obtained from patients treated with combinations of rifampin, isoniazid, and pyrazinamide and combinations of streptomycin, rifampin, isoniazid, and pyrazinamide.

Pregnancy-Teratogenic Effects

Category C. Rifampin has been shown to be teratogenic in rodents. Congenital malformations, primarily spina bifida were increased in the offspring of pregnant rats given rifampin during organogenesis at oral doses of 150 to 250 mg/kg/day (about 1 to 2 times the maximum recommended human dose based on body surface area comparisons). Cleft palate was increased in a dose-dependent fashion in fetuses of pregnant mice treated at oral doses of 50 to 200 mg/kg (about 0.2 to 0.8 times the maximum recommended human dose based on body surface area comparisons). Imperfect osteogenesis and embryotoxicity were also reported in pregnant rabbits given rifampin at oral doses up to 200 mg/kg/day (about 3 times the maximum recommended human dose based on body surface area comparisons). There are no adequate and well-controlled studies of rifampin in pregnant women. Rifampin has been reported to cross the placental barrier and appear in cord blood. Rifampin should be used during pregnancy only if the potential benefit justifies the potential risk to the fetus.

Pregnancy-Non-Teratogenic Effects

When administered during the last few weeks of pregnancy, rifampin can cause post-natal hemorrhages in the mother and infant for which treatment with vitamin K may be indicated.

Nursing Mothers

Because of the potential for tumorigenicity shown for rifampin in animal studies, a decision should be made whether to discontinue nursing or discontinue the drug, taking into account the importance of the drug to the mother.

Pediatric Use

See CLINICAL PHARMACOLOGY–Pediatrics; see also DOSAGE AND ADMINISTRATION.

Geriatric Use

Clinical studies of rifampin did not include sufficient numbers of subjects aged 65 and over to determine whether they respond differently from younger subjects. Other reported clinical experience has not identified differences in responses between the elderly and younger patients. Caution should therefore be observed in using rifampin in elderly patients. (See WARNINGS).

ADVERSE REACTIONS

Gastrointestinal

Heartburn, epigastric distress, anorexia, nausea, vomiting, jaundice, flatulence, cramps, and diarrhea have been noted in some patients. Although Clostridium difficile has been shown in vitro to be sensitive to rifampin, pseudomembranous colitis has been reported with the use of rifampin (and other broad spectrum antibiotics). Therefore, it is important to consider this diagnosis in patients who develop diarrhea in association with antibiotic use. Tooth discoloration (which may be permanent) may occur.

Hepatic

Transient abnormalities in liver function tests (e.g., elevations in serum bilirubin, alkaline phosphatase, serum transaminases) have been observed. Rarely, hepatitis or a shock-like syndrome with hepatic involvement and abnormal liver function tests has been reported.

Hematologic

Thrombocytopenia has occurred primarily with high dose intermittent therapy, but has also been noted after resumption of interrupted treatment. It rarely occurs during well supervised daily therapy. This effect is reversible if the drug is discontinued as soon as purpura occurs. Cerebral hemorrhage and fatalities have been reported when rifampin administration has been continued or resumed after the appearance of purpura.

Rare reports of disseminated intravascular coagulation have been observed.

Leukopenia, hemolytic anemia, and decreased hemoglobin have been observed.

Agranulocytosis has been reported very rarely.

Central Nervous System

Headache, fever, drowsiness, fatigue, ataxia, dizziness, inability to concentrate, mental confusion, behavioral changes, muscular weakness, pains in extremities, and generalized numbness have been observed.

Psychoses have been rarely reported.

Rare reports of myopathy have also been observed.

Ocular

Visual disturbances have been observed.

Endocrine

Menstrual disturbances have been observed.

Rare reports of adrenal insufficiency in patients with compromised adrenal function have been observed.

Renal

Elevations in BUN and serum uric acid have been reported. Rarely, hemolysis, hemoglobinuria, hematuria, interstitial nephritis, acute tubular necrosis, renal insufficiency, and acute renal failure have been noted. These are generally considered to be hypersensitivity reactions. They usually occur during intermittent therapy or when treatment is resumed following intentional or accidental interruption of a daily dosage regimen, and are reversible when rifampin is discontinued and appropriate therapy instituted.

Dermatologic

Cutaneous reactions are mild and self-limiting and do not appear to be hypersensitivity reactions. Typically, they consist of flushing and itching with or without a rash. More serious cutaneous reactions which may be due to hypersensitivity occur but are uncommon.

Hypersensitivity Reactions

Occasionally, pruritus, urticaria, rash, pemphigoid reaction, erythema multiforme including Stevens-Johnson Syndrome (see WARNINGS), toxic epidermal necrolysis, Drug Reaction with Eosinophilia and Systemic Symptoms syndrome, vasculitis, eosinophilia, sore mouth, sore tongue, and conjunctivitis have been observed.

Anaphylaxis has been reported rarely.

Miscellaneous

Edema of the face and extremities have been reported. Other reactions which have occurred with intermittent dosage regimens include "flu syndrome" (such as episodes of fever, chills, headache, dizziness, and bone pain), shortness of breath, wheezing, decrease in blood pressure and shock. The "flu syndrome" may also appear if rifampin is taken irregularly by the patient or if daily administration is resumed after a drug free interval.

To report SUSPECTED ADVERSE REACTIONS, contact VersaPharm Incorporated at 1-877-254-4381, or the FDA at 1-800-FDA-1088 or www.fda.gov/medwatch.

OVERDOSAGE

Signs and Symptoms

Nausea, vomiting, abdominal pain, pruritus, headache, and increasing lethargy will probably occur within a short time after ingestion; unconsciousness may occur when there is severe hepatic disease. Transient increases in liver enzymes and/or bilirubin may occur. Brownish-red or orange discoloration of the skin, urine, sweat, saliva, tears, and feces will occur, and its intensity is proportional to the amount ingested.

Liver enlargement, possibly with tenderness, can develop within a few hours after severe overdosage; bilirubin levels may increase and jaundice may develop rapidly. Hepatic involvement may be more marked in patients with prior impairment of hepatic function. Other physical findings remain essentially normal. A direct effect upon the hematopoietic system, electrolyte levels, or acid-base balance is unlikely.

Facial or periorbital edema has also been reported in pediatric patients. Hypotension, sinus tachycardia, ventricular arrhythmias, seizures and cardiac arrest were reported in some fatal cases.

Acute Toxicity

The minimum acute lethal or toxic dose is not well established. However, nonfatal acute overdoses in adults have been reported with doses ranging from 9 to 12 gm rifampin. Fatal acute overdoses in adults have been reported with doses ranging from 14 to 60 gm. Alcohol or a history of alcohol abuse was involved in some of the fatal and nonfatal reports. Nonfatal overdoses in pediatric patients ages 1 to 4 years old of 100 mg/kg for one to two doses has been reported.

Treatment

Intensive support measures should be instituted and individual symptoms treated as they arise. The airway should be secured and adequate respiratory exchange established. Since nausea and vomiting are likely to be present, gastric lavage within the first 2 to 3 hours after ingestion is probably preferable to induction of emesis. Following evacuation of the gastric contents, the instillation of activated charcoal slurry into the stomach may help absorb any remaining drug from the gastrointestinal tract. Antiemetic medication may be required to control severe nausea and vomiting.

Active diuresis (with measured intake and output) will help promote excretion of the drug.

For severe cases, extracorporeal hemodialysis may be required. If this is not available, peritoneal dialysis can be used along with forced diuresis.

DOSAGE AND ADMINISTRATION

Rifampin can be administered by the oral route (see INDICATIONS AND USAGE).

See CLINICAL PHARMACOLOGY for dosing information in patients with renal failure.

Tuberculosis

Adults: 10 mg/kg, in a single daily administration, not to exceed 600 mg/day.

Pediatric Patients: 10-20 mg/kg, not to exceed 600 mg/day.

It is recommended that oral rifampin be administered once daily, either 1 hour before or 2 hours after a meal with a full glass of water.

Rifampin is indicated in the treatment of all forms of tuberculosis. A three-drug regimen consisting of rifampin, isoniazid, and pyrazinamide [e.g., RIFATER®]^1 is recommended in the initial phase of short-course therapy which is usually continued for 2 months. The Advisory Council for the Elimination of Tuberculosis, the American Thoracic Society, and the Centers for Disease Control and Prevention recommend that either streptomycin or ethambutol be added as a fourth drug in a regimen containing isoniazid (INH), rifampin and pyrazinamide for initial treatment of tuberculosis unless the likelihood of INH resistance is very low. The need for a fourth drug should be reassessed when the results of susceptibility testing are known. If community rates of INH resistance are currently less than 4%, an initial treatment regimen with less than four drugs may be considered.

Following the initial phase, treatment should be continued with rifampin and isoniazid [RIFAMATE®]^2 for at least 4 months. Treatment should be continued for longer if the patient is still sputum or culture positive, if resistant organisms are present, or if the patient is HIV positive.

Meningococcal Carriers

Adults: For adults, it is recommended that 600 mg rifampin be administered twice daily for two days.

Pediatric Patients: Pediatric patients 1 month of age or older: 10 mg/kg (not to exceed 600 mg per dose) every 12 hours for two days.

Pediatric patients under 1 month of age: 5 mg/kg every 12 hours for two days.

Preparation of Extemporaneous Oral Suspension

For pediatric and adult patients in whom capsule swallowing is difficult or where lower doses are needed, a liquid suspension may be prepared as follows:

Rifampin 1% w/v suspension (10 mg/mL) can be compounded using Simple Syrup (Syrup NF), Simple Syrup (Humco Laboratories), SyrPalta® Syrup (Emerson Laboratories), or Raspberry Syrup (Humco Laboratories).

1. Empty the contents of four Rifampin 300 mg capsules or eight Rifampin 150 mg capsules onto a piece of weighing paper.
2. If necessary, gently crush the capsule contents with a spatula to produce a fine powder.
3. Transfer the rifampin powder blend to a 4-ounce amber glass or plastic (high density polyethylene [HDPE], polypropylene, or polycarbonate) prescription bottle.
4. Rinse the paper and spatula with 20 mL of one of the above mentioned syrup, and add the rinse to the bottle. Shake vigorously.
5. Add 100 mL of syrup to the bottle and shake vigorously.

This compounding procedure results in a 1% w/v suspension containing 10 mg rifampin/mL. Stability studies indicate that the suspension is stable when stored at room temperature (25 ± 3°C) or in a refrigerator (2-8°C) for four weeks. This extemporaneously prepared suspension must be shaken well prior to administration.

HOW SUPPLIED

Product: 50090-0964

NDC: 50090-0964-0 30 CAPSULE in a BOTTLE

NDC: 50090-0964-3 60 CAPSULE in a BOTTLE

REFERENCES

1. RIFATER® (rifampin, isoniazid, and pyrazinamide) is a registered trademark of Sanofi-Aventis U.S. LLC.
2. RIFAMATE® (rifampin and isoniazid) is a registered trademark of Sanofi-Aventis U.S. LLC.

Manufactured for:
VersaPharm Inc. – an Akorn Company
Lake Forest, IL 60045

Manufactured by:
Patheon Pharmaceuticals Inc.
Cincinnati, OH 45237

Revised November 2018
70036445